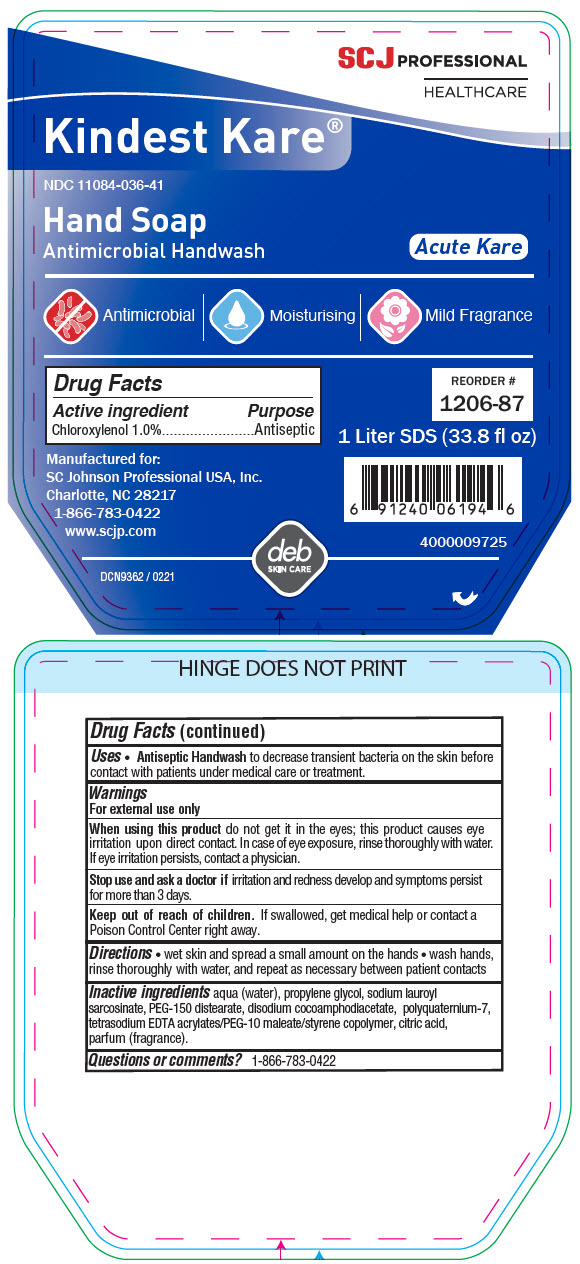 DRUG LABEL: Kindest Kare Hand 
NDC: 11084-036 | Form: SOAP
Manufacturer: SC Johnson Professional USA, Inc.
Category: otc | Type: HUMAN OTC DRUG LABEL
Date: 20241219

ACTIVE INGREDIENTS: CHLOROXYLENOL 1 g/100 mL
INACTIVE INGREDIENTS: WATER; PROPYLENE GLYCOL; SODIUM LAUROYL SARCOSINATE; PEG-150 DISTEARATE; DISODIUM COCOAMPHODIACETATE; POLYQUATERNIUM-7 (70/30 ACRYLAMIDE/DADMAC; 1600000 MW); EDETATE SODIUM; METHACRYLATE/METHOXY PEG-10 MALEATE/STYRENE COPOLYMER; CITRIC ACID MONOHYDRATE

Kindest Kare® Hand Soap
Antimicrobial Handwash

Drug Facts

Active ingredient

Chloroxylenol 1.0%

Purpose

Antiseptic

Uses

- Antiseptic Handwash to decrease transient bacteria on the skin before contact with patients under medical care or treatment.

Warnings

For external use only

When using this product do not get it in the eyes; this product causes eye irritation upon direct contact. In case of eye exposure, rinse thoroughly with water. If eye irritation persists, contact a physician.

Stop use and ask a doctor if irritation and redness develop and symptoms persist for more than 3 days.

Keep out of reach of children. If swallowed, get medical help or contact a Poison Control Center right away.

Directions

- wet skin and spread a small amount on the hands
- wash hands, rinse thoroughly with water, and repeat as necessary between patient contacts

Inactive ingredients

aqua (water), propylene glycol, sodium lauroyl sarcosinate, PEG-150 distearate, disodium cocoamphodiacetate, polyquaternium-7, tetrasodium EDTA acrylates/PEG-10 maleate/styrene copolymer, citric acid, parfum (fragrance).

Questions or comments?

1-866-783-0422

PRINCIPAL DISPLAY PANEL - 1 Liter Bottle Label

SCJ PROFESSIONAL
HEALTHCARE

Kindest Kare®

NDC 11084-036-41

Hand Soap
Antimicrobial Handwash

Acute Kare

Antimicrobial
Moisturising
Mild Fragrance

Manufactured for:
SC Johnson Professional USA, Inc.
Charlotte, NC 28217
1-866-783-0422
www.scjp.com

REORDER #
1206-87

1 Liter SDS (33.8 fl oz)

4000009725

DCN9362 / 0221

deb
SKIN CARE